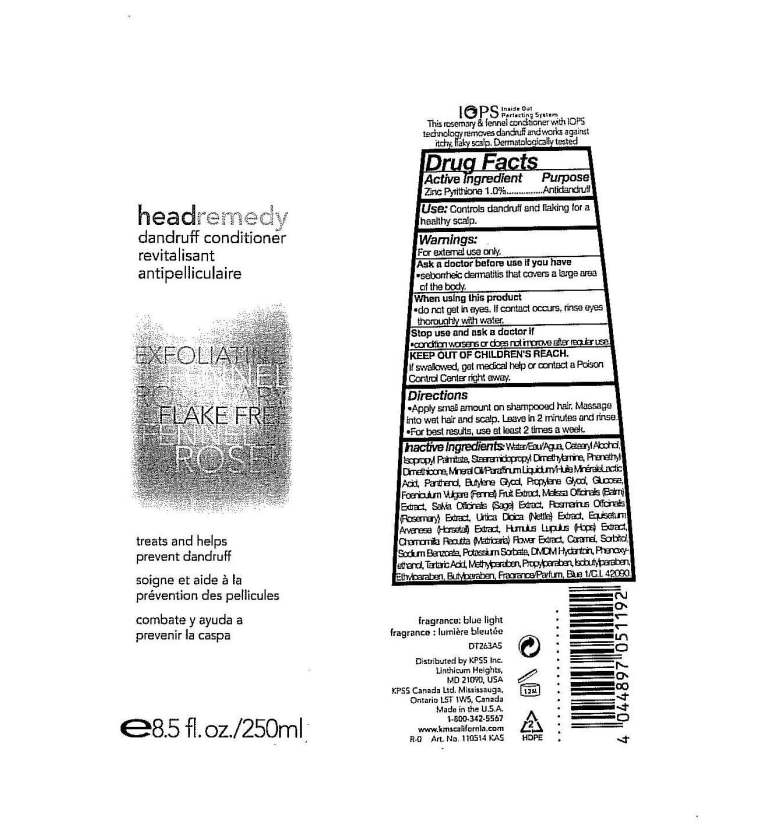 DRUG LABEL: Head Remedy Dandruff Conditioner
NDC: 25237-0516 | Form: EMULSION
Manufacturer: KPSS, Inc.
Category: otc | Type: HUMAN OTC DRUG LABEL
Date: 20100819

ACTIVE INGREDIENTS: PYRITHIONE ZINC 1.0 g/100 g

Drug Facts

Active Ingredient: Zinc Pyrithione 1.0%

Purpose: Antidandruff

INDICATIONS AND USAGE

Use: Controls dandruff and flaking for a healthy scalp.

Warnings: For external use only.

Ask a doctor before use if you have: seborrheic dermatitis that covers a large area of the body.

When using this product: do not get in eyes. If contact occurs, rinse eyes thoroughly with water.

Stop use and ask a doctor if: condition worsens or does not improve after regular use.

KEEP OUT OF REACH OF CHILDREN

Keep Out of Children's Reach: If swallowed, get medical help or contact a Poison Control Center right away.

DOSAGE AND ADMINISTRATION

Directions: Apply small amount on shampooed hair. Massage into wet hair and scalp. Leave in 2 minutes and rinse. For best results, use at least 2 times a week.

QUESTIONS

Distributed by KPSS Inc., Linthicum Heights, MD 21090 USA, 1-800-342-5567

PACKAGE LABEL

MM1: 8oz_dandruff_conditioner_label.jpg

INACTIVE INGREDIENT

water, cetearyl alcohol, isopropyl palmitate, stearamidopropyl dimethylamine, phenethyl dimethicone, mineral oil, lactic acid, panthenol, butylene glycol, propylene glycol, glucose, Foeniculum vulgare (Fennel) fruit extract, Melissa officinalis (Balm) extract, Salvia officinalis (Sage) extract, Rosmarinus officinalis (Rosemary) extract, Urtica dioica (Nettle) extract, Equisetum arvense (Horsetail) extract, Humulus lupulus (Hops) extract, Chamomilla recutita (Matricaria) flower extract, caramel, sorbitol, sodium benzoate, potassium sorbate, DMDM Hydantoin, phenoxyethanol, tartaric acid, methylparaben, propylparaben, isobutylparaben, ethylparaben, butylparaben, fragrance, blue 1